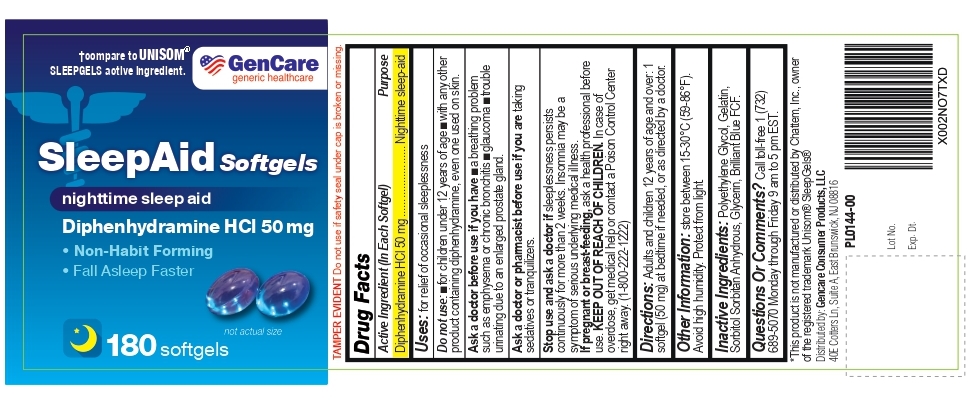 DRUG LABEL: SleepAid Softgels
NDC: 72090-023 | Form: CAPSULE, LIQUID FILLED
Manufacturer: PIONEER LIFE SCIENCES, LLC
Category: otc | Type: HUMAN OTC DRUG LABEL
Date: 20251229

ACTIVE INGREDIENTS: DIPHENHYDRAMINE HYDROCHLORIDE 50 mg/1 1
INACTIVE INGREDIENTS: POLYETHYLENE GLYCOL, UNSPECIFIED; GELATIN; SORBITOL; SORBITAN; GLYCERIN; FD&C BLUE NO. 1

SleepAid Softgels Diphenhydramine HCl 50 mg

Active Ingredient (In Each Softgel)

Diphenhydramine HCl 50 mg

Purpose

Nighttime sleep-aid

Uses

for relief of occasional sleeplessness

Do not use:

- for children under 12 years of age
- with any other product containing diphenhydramine, even one used on skin.

Ask a doctor before use if you have

- a breathing problem such as emphysema or chronic bronchitis
- glaucoma
- trouble urinating due to an enlarged prostate gland.

Ask a doctor or pharmacist before use if you are taking sedatives or tranquilizers.

Stop use and ask a doctor if sleeplessness persists continuously for more than 2 weeks. Insomnia may be a symptom of serious underlying medical illness.

PREGNANCY OR BREAST FEEDING

If pregnant or breast-feeding, ask a health professional before use.

KEEP OUT OF REACH OF CHILDREN. In case of overdose, get medical help or contact a Poison Control Center right away. (1-800-222-1222)

Directions:

Adults and children 12 years of age and over: 1 softgel (50 mg) at bedtime if needed, or as directed by a doctor.

Other Information:

store between 15-30°C (59-86°F). Avoid high humidity. Protect from light.

Inactive Ingredients:

Polyethylene Glycol, Gelatin, Sorbitol, Sorbitan Anhydrous, Glycerin, Brilliant Blue FCF.

Questions Or Comments?

Call toll-free 1 (732) 689-5070 Monday through Friday 9 am to 5 pm EST.

*This product is not manufactured or distributed by Chattem, Inc., owner of the registered trademark Unisom® SleepGels®

Distributed by: Gencare Consumer Products, LLC
40E Cotters Ln, Suite A, East Brunswick, NJ 08816